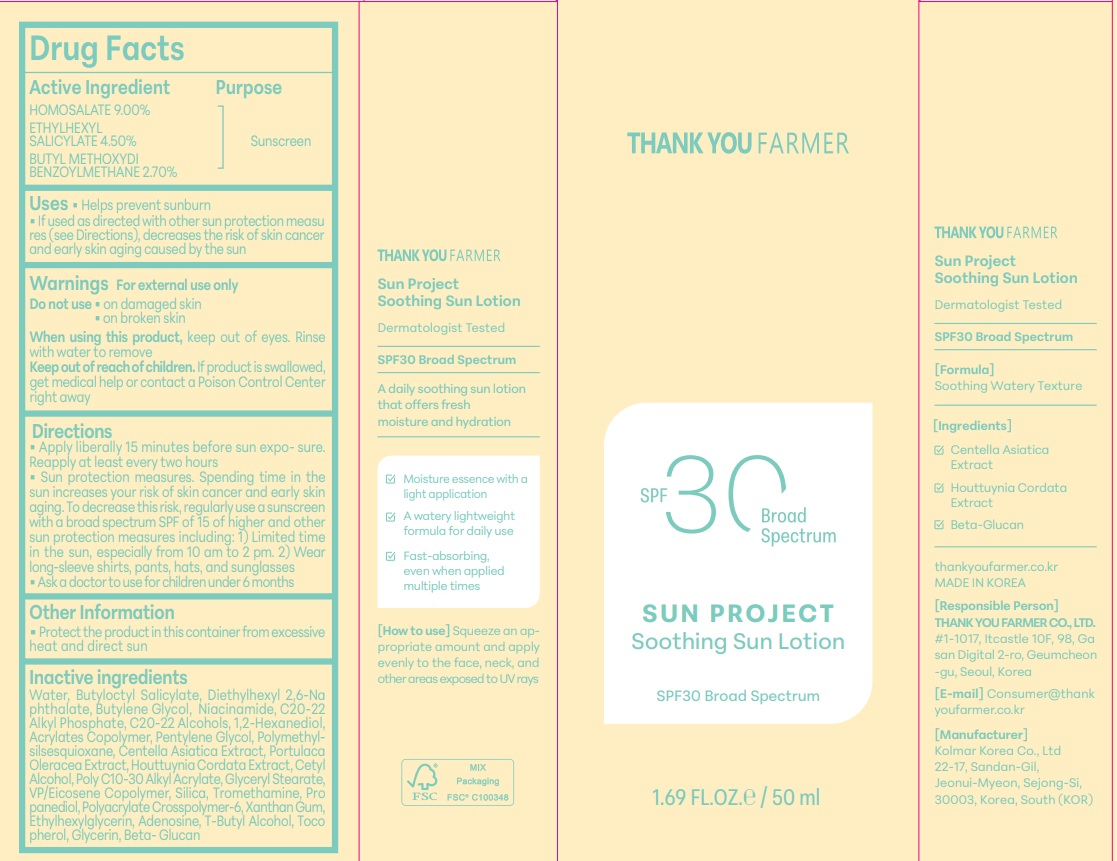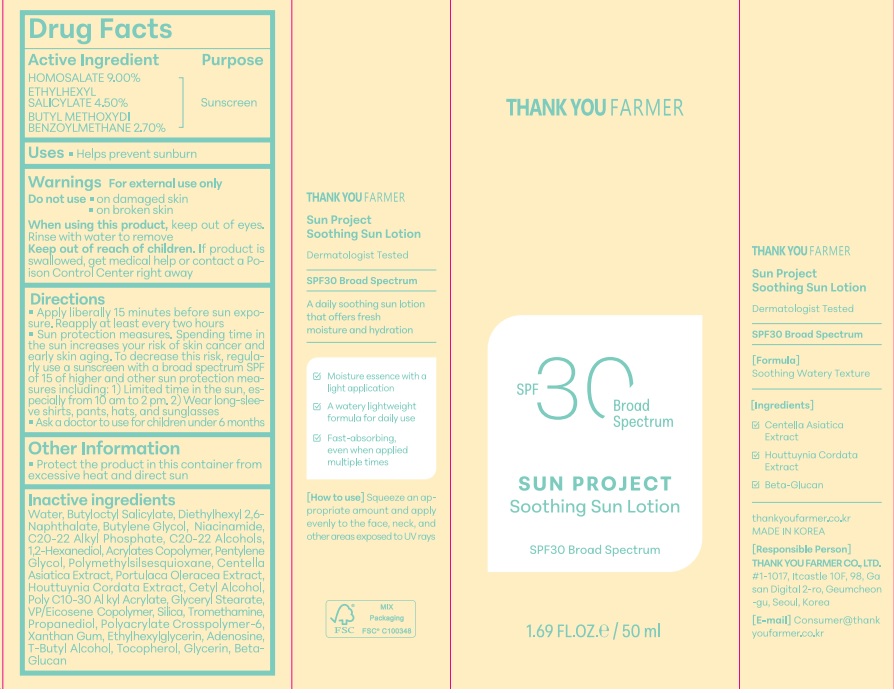 DRUG LABEL: THANKYOU FARMER Sun Project Soothing Sun
NDC: 70618-061 | Form: LOTION
Manufacturer: THANK YOU FARMER CO., LTD
Category: otc | Type: HUMAN OTC DRUG LABEL
Date: 20250313

ACTIVE INGREDIENTS: HOMOSALATE 4.5 g/50 mL; AVOBENZONE 1.35 g/50 mL; OCTISALATE 2.25 g/50 mL
INACTIVE INGREDIENTS: VINYLPYRROLIDONE/EICOSENE COPOLYMER; CENTELLA ASIATICA TRITERPENOIDS; TOCOPHEROL; 1,3-BETA-GLUCAN SYNTHASE COMPONENT FKS1; AMMONIUM ACRYLOYLDIMETHYLTAURATE; BUTYLENE GLYCOL; BUTYLOCTYL SALICYLATE; DIETHYLHEXYL 2,6-NAPHTHALATE; TERT-BUTYL ALCOHOL; HOUTTUYNIA CORDATA FLOWERING TOP; C20-22 ALKYL PHOSPHATE; C20-22 ALCOHOLS; SILICON DIOXIDE; XANTHAN GUM; BEHENYL ACRYLATE POLYMER; WATER; PROPANEDIOL; GLYCERYL STEARATE SE; 1,2-HEXANEDIOL; PENTYLENE GLYCOL; BUTYL ACRYLATE/METHYL METHACRYLATE/METHACRYLIC ACID COPOLYMER (18000 MW); NIACINAMIDE; POLYMETHYLSILSESQUIOXANE (11 MICRONS); GLYCERIN; TROMETHAMINE; ADENOSINE; ETHYLHEXYLGLYCERIN; PURSLANE; CETYL ALCOHOL

Active Ingredient-HOMOSALATE 9%, ETHYLHEXYL SALICYLATE-4.5%, BUTYL METHOXYDIBENZOYLMETHANE-2.7%

Purpose-Sunscreen

Purpose-Sunscreen, Uses-Helps prevent sunburn

Uses

Apply Liberally 15 minutes before sun exposure. Reapply at least every two hours, Sun Protection measures. Spending time in the sun increases your risk of skin cancer and early skin aging. To Decrease this risk, regularly use a sunscreen with a broad spectrum SPF of 15 of higher and other sun protection measures including: 1)Limited time in the sun, especially from 10am to 2pm. 2) Wear Long-sleeve shirts, pants, hats, and sunglasses. Ask a doctor to use for childer under 6 months.For external use only. Do not use on damaged skin & broken skin. When using this product, keep out of eyes. Rinse with water to remove. Keep out of reach of children. If product is swallowed medical help or contact a Poison Control Center right away

Warning

For external use only Do not use on damaged skin & broken skinWhen using this product, keep out of eyes. Rinse with water to remove. Keep out of reach of children. If product is swallowed medical help or contact a Poison Control Center right away

Do not use on damaged skin, on broken skin

Keep Out Of Reach of Children-Keep Out Of Reach of Children- If product is swallowed, get medical help or contact a Poison Control Center right away

Dosage & administration

Dosage & administration -Apply liberally 15 minutes before sun exposure. Reapply at least every two hours

Ask a doctor to use for children under 6 months

Inactive Ingredients

Inactive Ingredients-WATER, BUTYLOCTYL SALICYLATE, DIETHYLHEXYL 2,6-NAPHTHALATE, BUTYLENE GLYCOL,NIACINAMIDE, C20-22 ALKYL PHOSPHATE, C20-22 ALCOHOLS, 1,2-HEXANEDIOL, POLYMETHYLSILSESQUIOXANE, ACRYLATES COPOLYMER, PENTYLENE GLYCOL, CETYL ALCOHOL, POLY C10-30 ALKYL ACRYLATE, SILICA, VP/EICOSENE COPOLYMER, GLYCERYL STEARATE, TROMETHAMINE, PROPANEDIOL, POLYACRYLATE CROSSPOLYMER-6, XANTHAN GUM, ETHYLHEXYLGLYCERIN, ADENOSINE, PORTULACA OLERACEA EXTRACT, CENTELLA ASIATICA EXTRACT, HOUTTUYNIA CORDATA EXTRACT, T-BUTYL ALCOHOL, TOCOPHEROL, GLYCERIN, BETA-GLUCAN

Other Safety Information-Protect the product in this container from excessive heat and direct sun

Incations & usage

Helps prevent sunburn. If used as directed with other sun protection measures (see Directions), decreases the risk of skin cancer and early skin aging caused by the sun.

Package Label Principal Display Panel-Thank you Farmer SPF30 Broad Spectrum, Sun Project Soothing Sun Lotion SPF30 Broad Spectrum 1.69FL.OZ/50ML